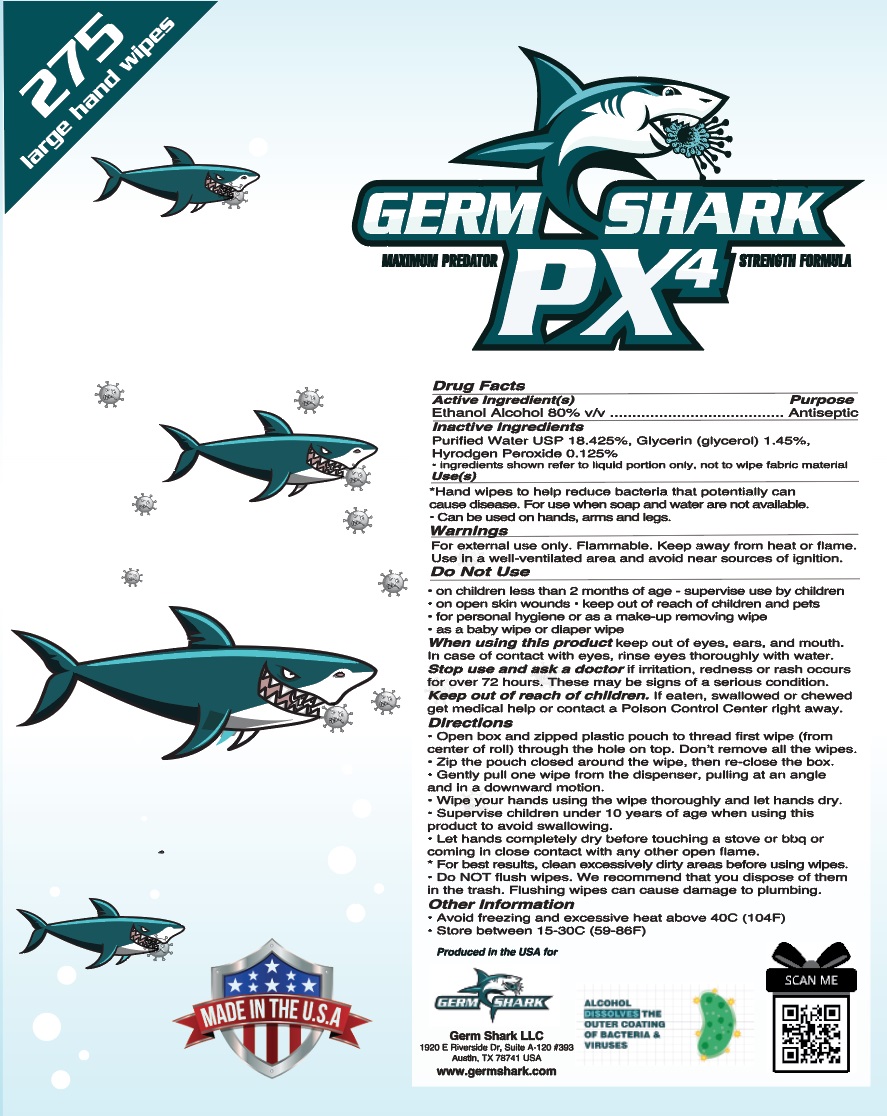 DRUG LABEL: Germ Shark PX4 Hand Jumbo Hand Sanitizing Wipes
NDC: 75158-003 | Form: CLOTH
Manufacturer: Germ Shark LLC
Category: otc | Type: HUMAN OTC DRUG LABEL
Date: 20200816

ACTIVE INGREDIENTS: ALCOHOL 0.8 mL/1 mL
INACTIVE INGREDIENTS: WATER; GLYCERIN; HYDROGEN PEROXIDE

Germ Shark PX4 Hand Jumbo Hand Sanitizing Wipes

Active Ingredient(s)

Ethanol Alcohol 80% v/v

Purpose

Antiseptic

Inactive Ingredients

Purified water USP 18.425%, Glycerin (glycerol) 1.45%, Hydrogen peroxide 0.125%

-ingredients shown refer to liquid portion only, not to wipe fabric material

Use(s)

Hand sanitizer to help reduce bacteria that potentially can cause disease. For use when soap and water are not available.

-Can be used on hands, arms and legs.

Warnings

For external use only. Flammable. Keep away from heat or flame.

Use in a well-ventilated area and avoid near sources of ignltion.

Do Not Use

- on children less than 2 months of age- supervise use by children
- on open skin wounds
- keep out of reach of children and pets
- for personal hygiene or as a make-up removing wipe
- as a baby wipe or diaper wipe

When using this product

keep out of eyes, ears, and mouth. In case of contact with eyes, rinse eyes thoroughly with water.

Stop use and ask a doctor

if irritation or redness or rash occurs. for over 72 hours. These may be signs of a serious condition.

Keep out of reach of children.

If eaten,swallowed or chewed get medical help or contact a Poison Control Center right away.

Directions

- Open box and zipped plastic pouch to thread first wipe (from center of roll) through the hole on top. Don't remove all the wipes.
- Zip the pouch closed around the wipe. then re-close the box.
- Gently pull one wipe from the dispenser, pulling at an angle and in a down ward motion.
- Supervise children under 10 years of age when using this product to avoid swallowing.
- Let hands completely dry before touching a stove or bbq or coming in close contact with any other open flame.
- For best results, clean excessively dirty areas before using wipes.
- Do Not fluh wipes. we recommended that you dispose of them in trash. Flushing wipes can cause damage to plumbing.

Other Information

- Avoid freezing and excessive heat above 40C (104F)
- Store between 15-30C (59-86F)